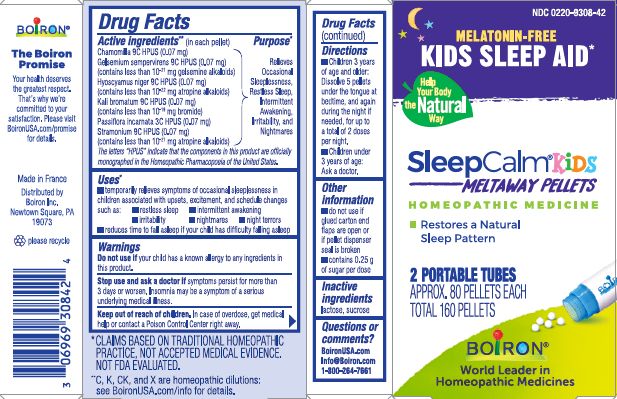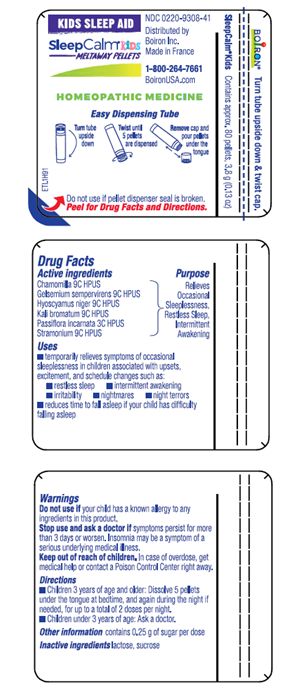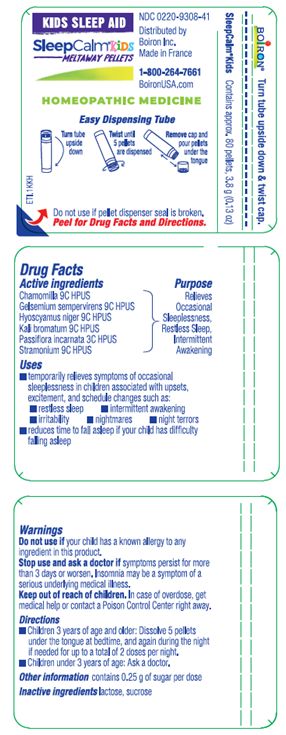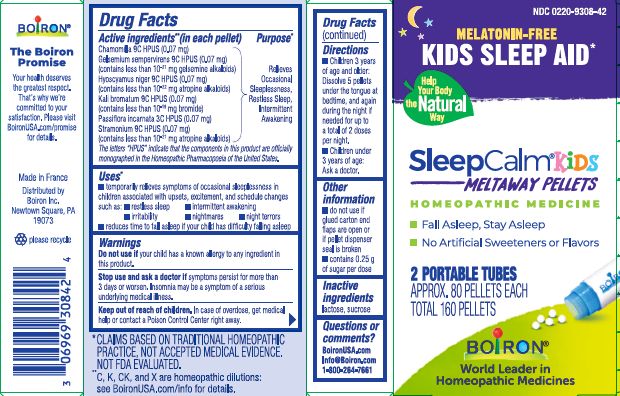 DRUG LABEL: SleepCalm
NDC: 0220-9308 | Form: PELLET
Manufacturer: Boiron
Category: homeopathic | Type: HUMAN OTC DRUG LABEL
Date: 20250307

ACTIVE INGREDIENTS: GELSEMIUM SEMPERVIRENS ROOT 9 [hp_C]/1 1; POTASSIUM BROMIDE 9 [hp_C]/1 1; HYOSCYAMUS NIGER 9 [hp_C]/1 1; PASSIFLORA INCARNATA FLOWERING TOP 3 [hp_C]/1 1; MATRICARIA CHAMOMILLA WHOLE 9 [hp_C]/1 1; DATURA STRAMONIUM 9 [hp_C]/1 1
INACTIVE INGREDIENTS: LACTOSE, UNSPECIFIED FORM; SUCROSE

SleepCalm Kids Pellet

Active ingredients** (in each pellet)

Chamomilla 9C HPUS (0.07 mg)

Gelsemium sempervirens 9C HPUS (0.07 mg)(contains less than 10^-21 mg gelsemine)

Hyoscyamus niger 9C HPUS (0.07 mg)(contains less than 10^-22 mg atropine alkaloids)

Kali bromatum 9C HPUS (0.07 mg)(contains less than 10^-19 mg bromide)

Passiflora incarnata 3C HPUS (0.07 mg)

Stramonium 9C HPUS (0.07 mg)(contains less than 10^-21 mg atropine alkaloids)

The letters "HPUS" indicate that the components in this product are officially monographed in the Homeopathic Pharmacopoeia of the United States.

Purpose*

Relieves Occasional Sleeplessness, Restless Sleep, Intermittent Awakening

Uses*

- temporarily relieves symptoms of occasional sleeplessness in children associated with upsets, excitement, and schedule changes such as:

- restless sleep
- intermittent awakening
- irritability
- nightmares
- night terrors

- reduces time to fall asleep if your child has difficulty falling asleep

Do not use if your child has a known allergy to any ingredients in this product.

Stop use and ask a doctor if symptoms persist for more than 3 days or worsen. Insomnia may be a symptom of a serious underlying medical illness.

Keep out of reach of children. In case of overdose, get medical help or contact a Poison Control Center right away.

Directions

- Children 3 years of age or older: Dissolve 5 pellets under the tongue at bedtime, and again during the night if needed, for up to a total of 2 doses per night.
- Children under 3 years of age: Ask a doctor.

INACTIVE INGREDIENT

lactose, sucrose

do not use if glued carton end flaps are open or if pellet dispenser seal is broken

contains 0.25 g of sugar per dose

2 PORTABLE TUBES

APPROX. 80 PELLETS EACH

TOTAL 160 PELLETS

Melatonin-Free

Kids Sleep Aid*

Tubes - contains approx. 80 pellets, 3.8g (0.13 oz)

Turn tube upside down, Twist until 5 pellets are dispensed, Remove cap and pour pellets under the tongue

*CLAIMS BASED ON TRADITIONAL HOMEOPATHIC PRACTICE NOT ACCEPTED MEDICAL EVIDENCE. NOT FDA EVALUATED.
**C,K,CK, and X are homeopathic dilutions: see BoironUSA.com/info for details.

QUESTIONS

BoironUSA.com

Info@Boiron.com

1-800-264-7661

Made in France

Distributed by Boiron Inc.

Newtown Square, PA 19073